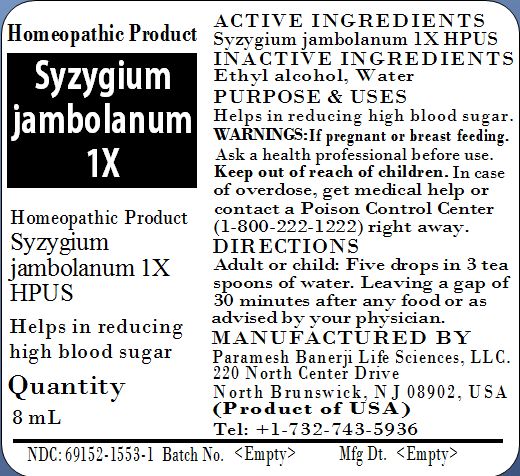 DRUG LABEL: Syzygium jambolanum 1X
NDC: 69152-1553 | Form: LIQUID
Manufacturer: Paramesh Banerji Life Sciences LLC
Category: homeopathic | Type: HUMAN PRESCRIPTION DRUG LABEL
Date: 20150605

ACTIVE INGREDIENTS: SYZYGIUM CUMINI SEED 1 [hp_X]/8 mL
INACTIVE INGREDIENTS: ALCOHOL; WATER

Active Ingredients

Syzygium jambolanum 1X HPUS

Inactive Ingredients

Ethyl alcohol, Water

Purpose

Helps in reducing high blood sugar

Uses

Helps in reducing high blood sugar

Warnings

If pregnant or breast feeding ask a health professional before use.

Keep out of reach of children. In case of overdose, get medical help or contact a Poison Control Center (1-800-222-1222) right away.

Direction

Adult or child: Five drops in 3 tea spoons of water, leaving a gap of 30 minutes from any food or as advised by your physician.

Manufactured by

Paramesh Banerji Life Sciences, LLC

220 North Center Drive

North Brunswick, NJ 08902, USA

Product of USA

Tel: +1-732-743-5936

Principal Display Panel

Homeopathic Product

Syzygium jambolanum 1X

Homeopathic Product

Syzygium jambolanum 1X HPUS

Helps in reducing high blood sugar

Quantity

8 mL